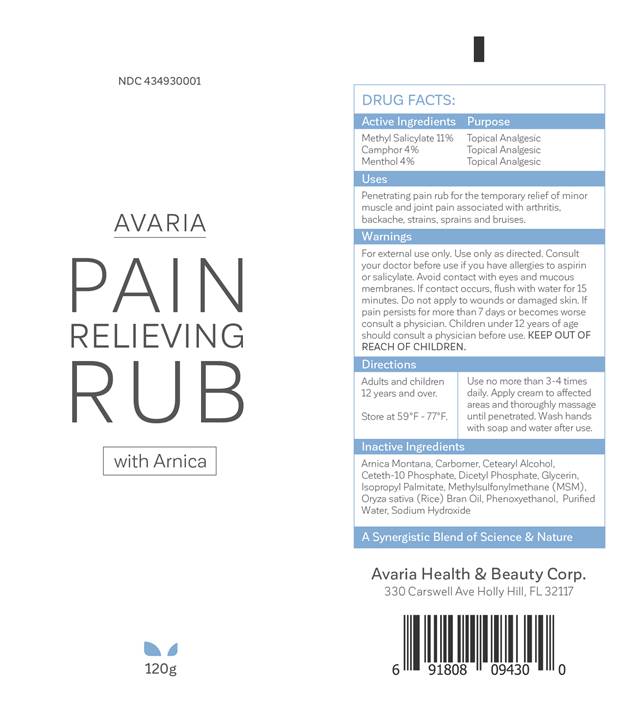 DRUG LABEL: Pain Relief Rub
NDC: 43493-0001 | Form: CREAM
Manufacturer: Avaria Health & Beauty Corp
Category: otc | Type: HUMAN OTC DRUG LABEL
Date: 20171115

ACTIVE INGREDIENTS: MENTHOL 4 g/100 g; CAMPHOR (NATURAL) 4 g/100 g; METHYL SALICYLATE 11 g/100 g
INACTIVE INGREDIENTS: GLYCERIN; SODIUM HYDROXIDE; CARBOMER INTERPOLYMER TYPE A (ALLYL SUCROSE CROSSLINKED); CETOSTEARYL ALCOHOL; CETETH-10 PHOSPHATE; DIHEXADECYL PHOSPHATE; DIMETHYL SULFONE; PHENOXYETHANOL; WATER; ARNICA MONTANA; RICE BRAN OIL; ISOPROPYL PALMITATE

Avaria Pain Relief Rub

ACTIVE INGREDIENT

Camphor 4%, Menthol 4%, Methyl Salicylate 11%

Uses

For the temporary relief of minor aches and pains of muscles and joints associated with arthritis, back ache, strains, bruises, and sprains.

Warnings

For external use only. Use only as directed. Consult your doctor before use if you have allergies to aspirin or salicylate. Avoid contact with eyes and mucous membranes. If contact occurs, flush with water for 15 minutes. Do not apply to wounds or damaged skin. If pain persists for more than 7 days or becomes worse consult a physician. Children under 12 years of age should consult a physician before use.

Directions

Adults and children 12 years of age and older: use no more than 3 to 4 times daily. Apply cream to affected areas and thoroughly massage until penetrated. Wash hands with soap and water after use.

Inactive ingredients

Arnica Montana, Carbomer, Cetearyl Alcohol, Ceteth-10 Phosphate, Dicetyl Phosphate, Glycerin, Isopropyl Palmitate, Methylsulfonylmethane (MSM), Oryza sativa (Rice) Bran Oil, Phenoxyethanol, Purified Water, Sodium Hydroxide

Purpose

Topical Analgesic.

Keep out of reach of children.

If swallowed, get medical help or contact a Poison Control Center right away.